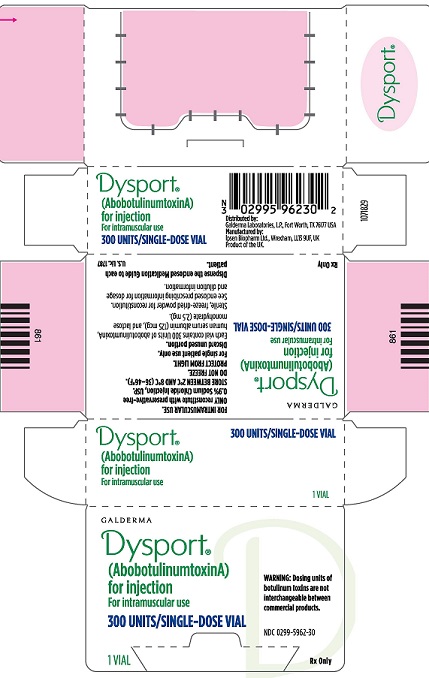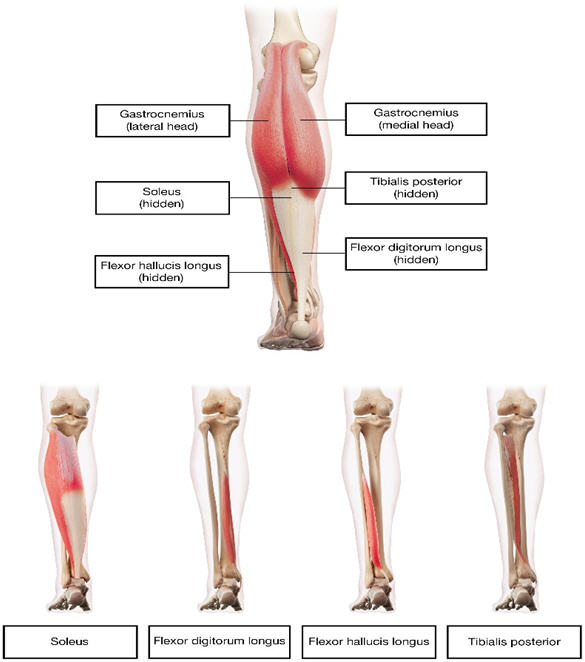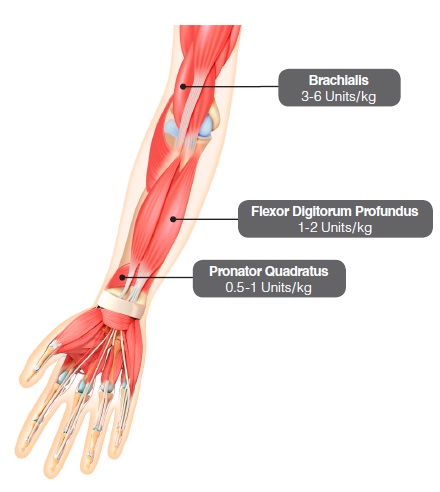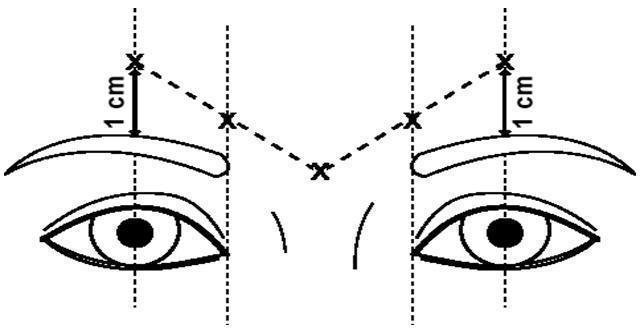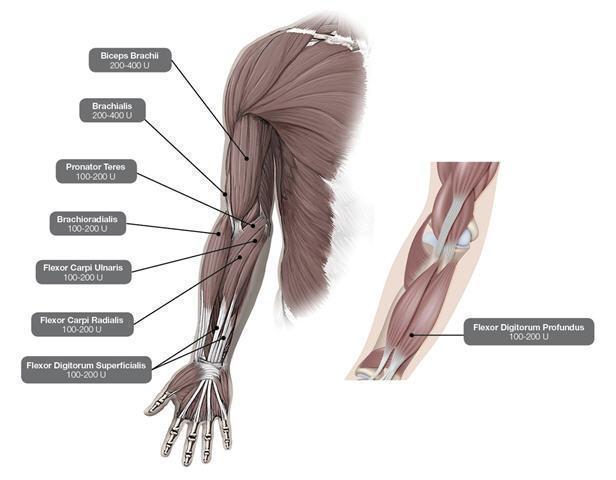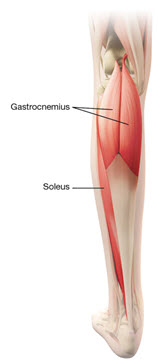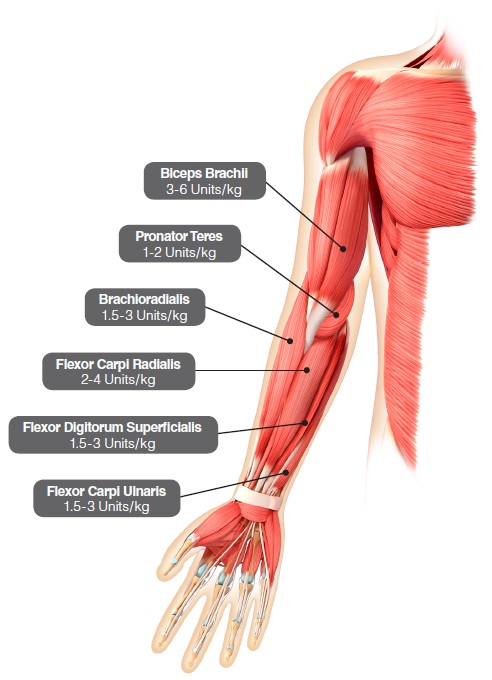 DRUG LABEL: Dysport
NDC: 0299-5962 | Form: INJECTION, POWDER, LYOPHILIZED, FOR SOLUTION
Manufacturer: Galderma Laboratories, L.P.
Category: prescription | Type: HUMAN PRESCRIPTION DRUG LABEL
Date: 20241024

ACTIVE INGREDIENTS: BOTULINUM TOXIN TYPE A 300 U/1 1
INACTIVE INGREDIENTS: ALBUMIN HUMAN; LACTOSE MONOHYDRATE

HIGHLIGHTS OF PRESCRIBING INFORMATION

These highlights do not include all the information needed to use DYSPORT safely and effectively. See full prescribing information for DYSPORT.
DYSPORT®(abobotulinumtoxinA) for injection, for intramuscular use
Initial U.S. Approval: April 2009

WARNING: DISTANT SPREAD OF TOXIN EFFECT

See full prescribing information for complete boxed warning

The effects of DYSPORT and all botulinum toxin products may spread from the area of injection to produce symptoms consistent with botulinum toxin effects. These symptoms have been reported hours to weeks after injection. Swallowing and breathing difficulties can be life-threatening and there have been reports of death. The risk of symptoms is probably greatest in children treated for spasticity but symptoms can occur in adults, particularly in those patients who have underlying conditions that would predispose them to these symptoms.(5.1)

RECENT MAJOR CHANGES

Dosage and Administration (2.2, 2.3, 2.5, 2.6) | 1/2023
Warning and Precautions (5.5, 5.10) | 09/2023

1 INDICATIONS AND USAGE

DYSPORT is an acetylcholine release inhibitor and neuromuscular blocking agent indicated for:

- the treatment of cervical dystonia in adults (1.1)
- the temporary improvement in the appearance of moderate to severe glabellar lines associated with procerus and corrugator muscle activity in adults < 65 years of age (1.2)
- The treatment of spasticity in patients 2 years of age and older (1.3)

2 DOSAGE AND ADMINISTRATION

Preparation of DYSPORT Solution for Administration (2.2)

- Once reconstituted, store in original container in a refrigerator 2°C to 8°C (36°F to 46°F) and use within 24 hours
- Do not freeze after reconstitution
- Reconstitution instructions are specific for the 300 Unit and 500 Unit vials
- Reconstituted DYSPORT is intended for intramuscular injection only. After reconstitution, DYSPORT should be used for only one injection session and for only one patient.

Cervical Dystonia (2.3)

• Initial dose is 500 Units given intramuscularly as a divided dose among the affected muscles
• Re-treatment every 12 to 16 weeks or longer, as necessary, based on return of clinical symptoms with doses administered between 250 and 1000 Units to optimize clinical benefit
• Re-treatment should not occur in intervals of less than 12 weeks
• Titrate in 250 Unit steps according to patient's response

Glabellar Lines (2.4)

- Administer a total dose of 50 Units, divided in five equal aliquots of 10 Units each, intramuscularly to affected muscles to achieve clinical effect
- Re-treatment should be administered no more frequently than every 3 months

Spasticity in Adults (2.5)

- Select dose based on muscles affected, severity of spasticity, and treatment and adverse reaction history botulinum toxins
- Dosing for upper limb spasticity: between 500 Units and 1000 Units
- Dosing for lower limb spasticity: up to 1500 Units
- The maximum recommended total dose per treatment session (upper and lower limb combined) in adults is 1500 Units
- Re-treatment, based on return of clinical symptoms, should not occur in intervals of less than 12 weeks

Spasticity in Pediatric Patients (2.6)

- Select dose based on the affected muscle, severity of spasticity, and treatment and adverse reaction history with all botulinum toxins.
- Recommended dosing for upper limb spasticity: 8 Units/kg to 16 Units/kg per limb. The maximum recommended total dose administered per treatment session must not exceed 16 Units/kg or 640 Units, whichever is lower.
- Recommended dosing for lower limb spasticity: 10 Units/kg to 15 Units/kg per limb. Total dose per treatment session must not exceed 15 Units/kg for unilateral lower limb injections, 30 Units/kg for bilateral injections, or 1000 Units, whichever is lower.
- The maximum recommended total dose per treatment session is 30 Units/kg or 1000 Units, whichever is lower. Re-treatment, based on return of clinical symptoms, should not occur in intervals of less than 3 months.

3 DOSAGE FORMS AND STRENGTHS

• For Injection: 300 Units or 500 Units lyophilized powder in a single-dose vial (3)

4 CONTRAINDICATIONS

• Hypersensitivity to:
• any botulinum toxin product or excipients (4, 5.3)
• cow's milk protein (4, 5.3)
• Infection at the proposed injection site(s) (4)

5 WARNINGS AND PRECAUTIONS

- The potency units of DYSPORT are not interchangeable with other preparations of botulinum toxin products (5.2)
- Immediate medical attention may be required in cases of respiratory, speech or swallowing difficulties (5.4)
- Recommended dose and frequency of administration should not be exceeded (5.5)
- Dry eye may occur with glabellar line treatment; if symptoms persist, consider referring patient to an ophthalmologist (5.6)
- Concomitant neuromuscular disorder may exacerbate clinical effects of treatment (5.7)

6 ADVERSE REACTIONS

Most commonly observed adverse reactions are (6.1):

Cervical Dystonia
(≥ 5%): muscular weakness, dysphagia, dry mouth, injection site discomfort, fatigue, headache, musculoskeletal pain, dysphonia, injection site pain and eye disorders

Glabellar Lines
(≥2%): nasopharyngitis, headache, injection site pain, injection site reaction, upper respiratory tract infection, eyelid edema, eyelid ptosis, sinusitis, nausea, and blood present in urine

Spasticity in Adults

- Upper limb spasticity (≥ 4%): muscular weakness
- Lower limb spasticity (≥ 5%): falls, muscular weakness, and pain in extremity

Spasticity in Pediatric Patients

- Upper limb spasticity (≥10%): upper respiratory tract infection and pharyngitis
- Lower limb spasticity ((≥10%): nasopharyngitis, cough, and pyrexia

To report SUSPECTED ADVERSE REACTIONS, contact Ipsen Biopharmaceuticals, Inc. at 855-463-5127 or FDA at 1-800-FDA-1088 or www.fda.gov/medwatch

7 DRUG INTERACTIONS

- Concomitant use of DYSPORT and aminoglycosides or other agents interfering with neuromuscular transmission or muscle relaxants, should be observed closely because the effect of DYSPORT may be potentiated (7.1, 7.4)
- Anticholinergic drugs may potentiate systemic anticholinergic effects (7.2)
- The effect of administering different botulinum neurotoxins during the course of treatment with DYSPORT is unknown (7.3)

8 USE IN SPECIFIC POPULATIONS

- Administer DYSPORT with care in elderly patients, reflecting the greater frequency of concomitant disease and other drug therapy (8.5)

FULL PRESCRIBING INFORMATION

WARNING: DISTANT SPREAD OF TOXIN EFFECT

Postmarketing reports indicate that the effects of DYSPORT and all botulinum toxin products may spread from the area of injection to produce symptoms consistent with botulinum toxin effects. These may include asthenia, generalized muscle weakness, diplopia, blurred vision, ptosis, dysphagia, dysphonia, dysarthria, urinary incontinence and breathing difficulties. These symptoms have been reported hours to weeks after injection. Swallowing and breathing difficulties can be life threatening and there have been reports of death. The risk of symptoms is probably greatest in children treated for spasticity but symptoms can also occur in adults treated for spasticity and other conditions, particularly in those patients who have underlying conditions that would predispose them to these symptoms. In unapproved uses and in approved indications, cases of spread of effect have been reported at doses comparable to or lower than the maximum recommended total dose [ see Warnings and Precautions (5.1)].

1 INDICATIONS AND USAGE

1.1 Cervical Dystonia

DYSPORT is indicated for the treatment of cervical dystonia in adults.

1.2 Glabellar Lines

DYSPORT is indicated for the temporary improvement in the appearance of moderate to severe glabellar lines associated with procerus and corrugator muscle activity in adults less than 65 years of age.

1.3 Spasticity

DYSPORT is indicated for the treatment of spasticity in patients 2 years of age and older.

2 DOSAGE AND ADMINISTRATION

2.1 Instructions for Safe Use

The potency units of DYSPORT are not interchangeable with other preparations of botulinum toxin products and, therefore, units of biological activity of DYSPORT cannot be compared to or converted into units of any other botulinum toxin products assessed with any other specific assay method [ see Warnings and Precautions (5.2) and Description (11)]. Reconstituted DYSPORT is intended for intramuscular injection only.

2.2 Preparation of Dysport Solution for Administration

DYSPORT is supplied as a dry powder, in single-dose 300 Unit and 500 Unit vials, which must be reconstituted with preservative-free 0.9% Sodium Chloride Injection, USP using aseptic technique prior to intramuscular injection. Table 1 provides dilution instructions for the 300 Unit and 500 Unit vials, depending on the desired final concentration. The desired final concentration after dilution varies depending on the indication (see Table 2for the recommended solution concentration after dilution).

Table 1: Dilution Instructions for DYSPORT Vials (500 Units and 300 Units)
Diluent [Preservative-free 0.9% Sodium Chloride Injection, USP Only] per 500 Unit Vial | Resulting Dose Unites per 0.1 mL | DIluent per 300 Unit Vial | Resulting Dose Units per 0.1 mL
1 mL | 50 Units | 0.6 mL | 50 Units
2 mL | 25 Units | -- | --
2.5 mL | 20 Units | 1.5 mL | 20 Units
-- | -- | 2.5 mL | 12 Units
5 mL‡ | 10 Units | 3 mL | 10 Units

Note: These dilutions are calculated for an injection volume of 0.1 mL. A decrease or increase in the DYSPORT dose is also possible by administering a smaller or larger injection volume (i.e., 0.05 mL (50% decrease in dose), 0.08% (20% decrease in dose) or 0.15 mL (50% increase in dose)).

‡ When using 5 mL of diluent for a 500 Unit vial of DYSPORT, no more than 2.5 mL of 0.9% Sodium Chloride Injection, USP should be introduced into the vial. Complete the following steps:

1. Reconstitute a 500 Unit vial of DYSPORT with 2.5 mL of Preservative-free 0.9% Sodium Chloride Injection, USP, gently mix, and set the vital aside.
2. Withdraw 2.5 mL of Preservative-free 0.9 Sodium Chloride Infection, USP into a 5 mL syringe
3. Take the 5 mL syringe with 2.5 ml Preservative-free Sodium Chloride Injection, USP and draw up the DYSPORT solution from the reconstituted vial without inverting and mix gently. The resulting concentration will be 10 units/0.1 mL
4. Use immediately after reconstitution in the syringe. Dispose of any unused 0.9% Sodium Chloride Injection, USP.

Using an appropriately sized sterile syringe, needle and aseptic technique, draw up the required amount of sterile, preservative-free 0.9% Sodium Chloride Injection, USP (see Table 1). Insert the needle into the DYSPORT vial. The partial vacuum will begin to pull the saline into the vial. Any remaining required saline should be expressed into the vial manually. Do not use the vial if no partial vacuum is observed. Swirl gently to dissolve. Parenteral drug products should be inspected visually for particulate matter and discoloration prior to administration.
Reconstituted DYSPORT should be a clear, colorless solution, free of particulate matter, otherwise it should not be injected. Expel any air bubbles in the syringe barrel. Remove the needle used to reconstitute the product and attach an appropriately sized new sterile needle for injection.

After reconstitution, DYSPORT should be used for only one injection session and for only one patient. Discard any unused portion. Once reconstituted, unused DYSPORT may be stored in the original container, in a refrigerator at 2°C to 8°C (36°F to 46°F), protected from light for up to 24 hours until time of use. It must be discarded if not used within 24 hours. Do not freeze reconstituted DYSPORT. Discard the vial and needle in accordance with local regulations.

Table 2: Recommended Solution Concentration and Dosing Range of DYSPORT by Indication
Indication | Recommended Concentration | Recommended DYSPORT Dose
Cervical Dystonia, Adults | 50 Units/0.1 mL or 25 Units/0.1 mL | 500 Units to 1000 Units
Glabellar Lines, Adults | 12 Units/0.1 mL or 20 Units/0.1 mL | 50 Units, divided in five equal aliquots of 10 Units (0.08 mL) each or 50 Units, divided in five equal aliquots of 10 Units (0.05 mL) each
Spasticity, Adults* | 10 Units/0.1 mL or 20 Units/0.1 mL | Upper Limb: 500 Units to 1000 Units Lower Limb: 1000 Units to 1500 Units Maximum total dose per treatment session = 1500 Units
Spasticity, Pediatric Patients‡ | 20 Units/0.1 mL or 50 Units/0.1 mL** | Upper Limb: 8 Units/kg to 16 Units/kg per limb; - Maximum total dose per treatment session = 16 Units/kg or 640 Units, whichever is lower; Lower Limb: 10 Units/kg to 15 Units/kg per limb; - Maximum total dose per treatment session for unilateral limb injections = 15 Units/kg or 1000 Units, whichever is lower - Maximum total dose per treatment session for bilateral limb injections = 30 Units/kg or 1000 Units, whichever is lower; Maximum total dose per treatment session = 30 Units/kg or 1000 Units, whichever is lower

* No more than 1 mL should generally be administered at any single injections site
‡No more than 0.5 mL of DYSPORT should be administered in any single injection site
** Further dilution with preservative-free 0.9% Sodium Chloride Injection, USP, may be required to achieve the final volume for injection.

2.3 Dosing in Cervical Dystonia

The recommended initial dose of DYSPORT for the treatment of cervical dystonia in adults is 500 Units given intramuscularly as a divided dose among affected muscles in patients with or without a history of prior treatment with botulinum toxin. (A description of the average DYSPORT dose and percentage of total dose injected into specific muscles in the pivotal clinical trials can be found in Table 15 of Section 14.1, Clinical Studies – Cervical Dystonia.) Limiting the dose injected into the sternocleidomastoid muscle may reduce the occurrence of dysphagia. Clinical studies with DYSPORT in cervical dystonia suggest that the peak effect occurs between two and four weeks after injection. Simultaneous guided injection of DYSPORT with EMG and/or ultrasound may be helpful in locating active muscles.

Dose Modification

Where dose modification is necessary for the treatment of cervical dystonia, uncontrolled open-label studies suggest that dose adjustment can be made in 250 Unit steps according to the individual patient's response, with re-treatment every 12 weeks or longer, as necessary, based on return of clinical symptoms. Uncontrolled open-label studies also suggest that the total dose administered in a single treatment should be between 250 Units and 1000 Units. Re-treatment, if needed, should not occur in intervals of less than 12 weeks. Doses above 1000 Units have not been systematically evaluated.

2.4 Dosing in Glabellar Lines

The dose of DYSPORT for the treatment of glabellar lines in adults is a total of 50 Units given intramuscularly in five equal aliquots of 10 Units each to achieve clinical effect (see Figure 1).

The clinical effect of DYSPORT may last up to four months. Repeat dosing in clinical studies demonstrated continued efficacy with up to four repeated administrations. It should be administered no more frequently than every three months. When used for re-treatment, DYSPORT should be reconstituted and injected using the same techniques as the initial treatment.

Injection Technique

Glabellar facial lines arise from the activity of the lateral corrugator and vertical procerus muscles. These can be readily identified by palpating the tensed muscle mass while having the patient frown. The corrugator depresses the skin creating a "furrowed" vertical line surrounded by tensed muscle (i.e., frown lines). The location, size, and use of the muscles vary markedly among individuals. Physicians administering DYSPORT must understand the relevant neuromuscular and/or orbital anatomy of the area involved and any alterations to the anatomy due to prior surgical procedures.

Risk of ptosis can be mitigated by careful examination of the upper lid for separation or weakness of the levator palpebrae muscle (true ptosis), identification of lash ptosis, and evaluation of the range of lid excursion while manually depressing the frontalis to assess compensation.

In order to reduce the complication of ptosis, the following steps should be taken:

- Avoid injection near the levator palpebrae superioris, particularly in patients with larger brow depressor complexes.
- Medial corrugator injections should be placed at least 1 centimeter above the bony supraorbital ridge.
- Ensure the injected volume/dose is accurate and where feasible kept to a minimum.
- Do not inject toxin closer than 1 centimeter above the central eyebrow.

To inject DYSPORT, advance the needle through the skin into the underlying muscle while applying finger pressure on the superior medial orbital rim. Inject patients with a total of 50 Units in five equally divided aliquots. Using an appropriately sized needle, inject 10 Units of DYSPORT into each of five sites, two in each corrugator muscle, and one in the procerus muscle (see Figure 1).

Figure 1

2.5 Dosing in Spasticity in Adults

Dosing in initial and subsequent treatment sessions should be tailored to the individual based on the size, number and location of muscles involved, severity of spasticity, the presence of local muscle weakness, the patient's response to previous treatment, and/or adverse reaction history with botulinum toxins.

No more than 1 mL should generally be administered at any single injection site. The maximum recommended total dose (upper and lower limb combined) of DYSPORT for the treatment of spasticity in adults is 1500 Units.

Although actual location of the injection sites can be determined by palpation, the use of injection guiding technique (e.g., electromyography, electrical stimulation, or ultrasound) is recommended to target the injection sites.

Upper Limb Spasticity

In the clinical trial that assessed the efficacy and safety of DYSPORT for treatment of upper limb spasticity in adults [ see Clinical Studies (14.3)], doses of 500 Units and 1000 Units were divided among selected muscles at a given treatment session (see Table 3and Figure 2).

Table 3: DYSPORT Dosing by Muscle for Upper Limb Spasticity in Adults
Muscles Injected | Recommended Dose DYSPORT | Recommended Number of Injection(s) per Muscle
Flexor carpi radialis (FCR); Flexor carpi ulnaris (FCU) | 100 Units to 200 Units; 100 Units to 200 Units | 1 to 2; 1 to 2
Flexor digitorum profundus (FDP); Flexor digitorum superficialis (FDS) | 100 Units to 200 Units; 100 Units to 200 Units | 1 to 2; 1 to 2
Brachialis; Brachioradialis; Biceps Brachii (BB); Pronator Teres | 200 Units to 400 Units; 100 Units to 200 Units; 200 Units to 400 Units; 100 Units to 200 Units | 1 to 2; 1 to 2; 1 to 2; 1

Figure 2: Muscles for Injection for Upper Limb Spasticity in Adults

Repeat DYSPORT treatment should be administered when the effect of a previous injection has diminished, but no sooner than 12 weeks after the previous injection. A majority of patients in clinical studies were retreated between 12-16 weeks; however some patients had a longer duration of response (i.e. 20 weeks). The degree and pattern of muscle spasticity at the time of re-injection may necessitate alterations in the dose of DYSPORT and muscles to be injected. Clinical improvement may be expected one week after administration of DYSPORT.

Lower Limb Spasticity

In the clinical trial that assessed the efficacy and safety of DYSPORT for treatment of lower limb spasticity in adults [ see Clinical Studies (14.3)], doses of 1000 Units and 1500 Units were divided among selected muscles at a given treatment session (see Table 4 and Figure 3).

Table 4: DYSPORT Dosing by Muscle for Lower Limb Spasticity in Adults
Muscles Injected | Recommended DYSPORT Dose | Recommended Number of Injection Sites per Muscle
Distal Muscles
Gastrocnemius
Medial head | 100 Units to 150 Units | 1
Lateral head | 100 Units to 150 Units | 1
Soleus | 330 Units to 500 Units | 3
Tibialis posterior | 200 Units to 300 Units | 2
Flexor digitorum longus | 130 Units to 200 Units | 1 to 2
Flexor halluces longus | 70 Units to 200 Units | 1

Figure 3: Muscle for Injection for Lower Limb Spasticity in Adults

Repeat DYSPORT treatment should be administered when the effect of a previous injection has diminished, but no sooner than 12 weeks after the previous injection. A majority of patients in clinical studies were retreated between 12-16 weeks. The degree and pattern of muscle spasticity at the time of re-injection may necessitate alterations in the dose of DYSPORT and muscles to be injected.

2.6 Dosing in Spasticity in Pediatric Patients

DYSPORT dosing for spasticity in pediatric patients is based on Units per kilogram of body weight. To calculate the total units of DYSPORT required for treatment of one limb, select the dose of DYSPORT in Units/kg and the body weight (kg) of the patient (see Tables 5 and 6). Dosing in initial and sequential treatment sessions should be tailored to the individual patient based on the size, number and location of muscles involved, severity of spasticity, the presence of local muscle weakness, the patient’s response to previous treatment, and/or adverse reaction history with botulinum toxins.
No more than 0.5 mL should generally be administered at any single injection site. The maximum recommended total dose of DYSPORT in a single treatment session for spasticity in pediatric patients 2 years or older is 30 Units/kg or 1000 Units in a 3-month interval.
Although actual location of the injection sites can be determined by palpation, the use of injection guiding technique (e.g., electromyography or electrical stimulation, or ultrasound) is recommended to target the injection sites.
Upper Limb Spasticity in Pediatric Patients 2 Years of Age and Older
In the clinical trial that assessed the efficacy and safety of DYSPORT for treatment of upper limb spasticity in pediatric patients 2 years of age or older with a weight of at least 10 kg [ see Clinical Studies (14.4)], doses of 8 Units/kg or 16 Units/kg were divided among selected muscles of the target upper limb at a given treatment session (see Table 5 and Figure 4).
Table 5 describes the recommended Units/kg dose of DYSPORT per muscle. The maximum recommended total dose of DYSPORT administered for treatment of upper limb spasticity must not exceed 16 Units/kg or 640 Units, whichever is lower.

Table 5: DYSPORT Dosing by Muscle for Upper Limb Spasticity in Pediatric Patients
Muscle | Recommended Dose Range per muscle per upper limb (units/kg Body Weight) | Number of injection sites per muscle
Brachialis | 3 Units/kg to 6 Units/kg | Up to 2
Brachioradialis | 1.5 Units/kg to 3 Units/kg | 1
Biceps brachii | 3 Units/kg to 6 Units/kg | Up to 2
Pronator teres | 1 Units/kg to 2 Units/kg | 1
Prontator quadratus | 0.5 Unit/kg to 1 Units/kg | 1
Flexor carpi radialis (FCR) | 2 Units/kg to 4 Units/kg | Up to 2
Flexor carpi ulnaris (FCU) | 1.5 Units/kg to 3 Units/kg | 1
Flexor digitorum profundus (FDP) | 1 Units/kg to 2 Units/kg | 1
Flexor digitorum superficialis (FDS) | 1.5 Units/kg to 3 Units/kg | Up to 4
Total dose | 8 Units/kg to 16 Units/kg in upper limbs (and not exceeding 640 Units)

Figure 4: Muscles for Injection for Upper Limb Spasticity in Pediatric Patients

Repeat DYSPORT treatment should be administered when the effect of a previous injection has diminished but no sooner than 16 weeks after the previous injection. A majority of patients in the clinical study were retreated between 16-28 weeks; however, some patients had a longer duration of response (i.e., 34 weeks or more). The degree and pattern of muscle spasticity at the time of re-injection may necessitate alterations in the dose of DYSPORT and muscles to be injected.
Lower Limb Spasticity in Pediatric Patients 2 Years of Age and Older
In the clinical trial that assessed the efficacy and safety of DYSPORT for treatment of lower limb spasticity in pediatric patients 2 years of age or older [see Clinical Studies (14.4)], doses of 10 Units/kg to 15 Units/kg were divided among selected muscles of the target lower limb at a given treatment session (see Table 6 and Figure 5).
Table 6 describes the recommended Units/kg dose of DYSPORT per muscle of the Gastrocnemius-Soleus Complex (GSC). The recommended total DYSPORT dose per treatment session is 10 Units/kg to 15 Units/kg for unilateral lower limb injections or 20 Units/kg to 30 Units/kg for bilateral lower limb injections. However, the total dose of DYSPORT administered in a 3-month interval must not exceed 15 Units/kg for unilateral lower limb injections, 30 Units/kg for bilateral lower limb injections, or 1000 units, whichever is lower. The total dose administered should be divided between the affected spastic muscles of the lower limb(s). When possible, the dose should be distributed across more than 1 injection site in any single muscle (see Table 6).

Table 6. DYSPORT Dosing by Muscle for Lower Limb Spasticity in Pediatric Patients
Muscle Injected | Recommended DYSPORT Dose Range per muscle per leg (Units/kg Body Weight) | Recommended number of injections per muscle
Gastrocnemius | 6 Units/kg to 9 Units/kg [the listed individual doses to be injected in the muscles can be used within the range mentioned without exceeding 15 Units/kg total dose for unilateral injection or 30 Units/kg for bilateral injections or 1000 Units whichever is lower.] | Up to 4
Soleus | 4 Units/kg to 6 Units/kg | Up to 2
Total | 10 Units/kg to 15 Units/kg divided across both muscles | Up to 6

Figure 5: Muscles for Injection for Lower Limb Spasticityin Pediatric Patients

Although actual location of the injection sites can be determined by palpation, the use of injection guiding technique (e.g. electromyography or electrical stimulation or ultrasound) is recommended to target the injection sites.

Repeat DYSPORT treatment should be administered when the effect of a previous injection has diminished but no sooner than 12 weeks after the previous injection. A majority of patients in the clinical studies were retreated between 16-22 weeks, however; some had a longer duration of response. The degree and pattern of muscle spasticity and overall clinical benefit at the time of re-injection may necessitate alterations in the dose of DYSPORT and muscles to be injected.

The safety and effectiveness of DYSPORT injected into proximal muscles of the lower limb for the treatment of spasticity in pediatric patients has not been established.

3 DOSAGE FORMS AND STRENGTHS

For injection: 300 Units or 500 Units of lyophilized powder in a single-dose vial for reconstitution with preservative-free 0.9% Sodium Chloride Injection, USP.

4 CONTRAINDICATIONS

DYSPORT is contraindicated in patients with:

- Known hypersensitivity to any botulinum toxin products, cow's milk protein, or to any of the components in the formulation [ see Warnings and Precautions (5.3)] . This product may contain trace amounts of cow's milk protein [ see Description (11)] .
- Infection at the proposed injection site(s).

5 WARNINGS AND PRECAUTIONS

5.1 Spread of Toxin Effect

Postmarketing safety data from DYSPORTand other approved botulinum toxins suggest that botulinum toxin effects may, in some cases, be observed beyond the site of local injection. The symptoms are consistent with the mechanism of action of botulinum toxin and may include asthenia, generalized muscle weakness, diplopia, blurred vision, ptosis, dysphagia, dysphonia, dysarthria, urinary incontinence and breathing difficulties. These symptoms have been reported hours to weeks after injection. Swallowing and breathing difficulties can be life-threatening and there have been reports of death related to spread of toxin effects. The risk of symptoms is probably greatest in children treated for spasticity but symptoms can also occur in adults treated for spasticity and other conditions, particularly in those patients who have underlying conditions that would predispose them to these symptoms. In unapproved uses and approved indications, symptoms consistent with spread of toxin effect have been reported at doses comparable to or lower than the maximum recommended total dose.

5.2 Lack of Interchangeability between Botulinum Toxin Products

The potency Units of DYSPORT are specific to the preparation and assay method utilized. They are not interchangeable with other preparations of botulinum toxin products and, therefore, units of biological activity of DYSPORT cannot be compared to or converted into units of any other botulinum toxin products assessed with any other specific assay method [see Description (11)].

5.3 Hypersensitivity Reactions

Serious hypersensitivity reactions have been reported with DYSPORT. Hypersensitivity reactions include anaphylaxis, serum sickness, urticaria, soft tissue edema, and dyspnea. If such a serious hypersensitivity reaction occurs, discontinue further injection of DYSPORT and institute appropriate medical therapy immediately.

5.4 Dysphagia and Breathing Difficulties

Treatment with DYSPORT and other botulinum toxin products can result in swallowing or breathing difficulties. Patients with pre-existing swallowing or breathing difficulties may be more susceptible to these complications. In most cases, this is a consequence of weakening of muscles in the area of injection that are involved in breathing or swallowing. When distant effects occur, additional respiratory muscles may be involved [ see Boxed Warning and Warnings and Precautions (5.2)] .

Deaths as a complication of severe dysphagia have been reported after treatment with botulinum toxin. Dysphagia may persist for several weeks and require use of a feeding tube to maintain adequate nutrition and hydration. Aspiration may result from severe dysphagia and is a particular risk when treating patients in whom swallowing or respiratory function is already compromised.

Treatment of cervical dystonia with botulinum toxins may weaken neck muscles that serve as accessory muscles of ventilation. This may result in a critical loss of breathing capacity in patients with respiratory disorders who may have become dependent upon these accessory muscles. There have been post-marketing reports of serious breathing difficulties, including respiratory failure.
Patients treated with botulinum toxin may require immediate medical attention should they develop problems with swallowing, speech or respiratory disorders. These reactions can occur within hours to weeks after injection with botulinum toxin [see Boxed Warning, Warnings and Precautions (5.2), Adverse Reactions (6.1), Clinical Pharmacology (12.2)].

5.5 Facial Anatomy in the Treatment of Glabellar Lines

Caution should be exercised when administering DYSPORT to patients with surgical alterations to the facial anatomy, marked facial asymmetry, inflammation at the injection site(s), ptosis, excessive dermatochalasis, deep dermal scarring, thick sebaceous skin [ see Dosage and Administration (2.4)] or the inability to substantially lessen glabellar lines by physically spreading them apart [ see Clinical Studies (14.2)] .

Do not exceed the recommended dosage and frequency of administration of DYSPORT. In clinical trials, subjects who received a higher dose of DYSPORT had an increased incidence of eyelid ptosis.

5.6 Dry Eye with the Treatment of Glabellar Lines

Dry eye has been reported with the use of DYSPORT in the treatment of glabellar lines [see Adverse Reactions (6.3)]. Reduced tear production, reduced blinking, and corneal disorders, may occur with use of botulinum toxins, including DYSPORT. If symptoms of dry eye (e.g., eye irritation, photophobia, or visual changes) persist, consider referring patient to an opththalmologist [ see Boxed Warning and Warnings and Precautions 5.2].

5.7 Pre-existing Neuromuscular Disorders

Individuals with peripheral motor neuropathic diseases, amyotrophic lateral sclerosis or neuromuscular junction disorders (e.g., myasthenia gravis or Lambert-Eaton syndrome) should be monitored particularly closely when given botulinum toxin. Patients with neuromuscular disorders may be at increased risk of clinically significant effects including severe dysphagia and respiratory compromise from typical doses of DYSPORT [ see Adverse Reactions (6.1)] .

5.8 Human Albumin and Transmission of Viral Diseases

This product contains albumin, a derivative of human blood. Based on effective donor screening and product manufacturing processes, it carries an extremely remote risk for transmission of viral diseases and variant Creutzfeldt-Jakob disease (vCJD). There is a theoretical risk for transmission of Creutzfeldt-Jakob disease (CJD), but if that risk actually exists, the risk of transmission would also be considered extremely remote. No cases of transmission of viral diseases, CJD, or vCJD have ever been identified for licensed albumin or albumin contained in other licensed products.

5.9 Intradermal Immune Reaction

The possibility of an immune reaction when injected intradermally is unknown. The safety of DYSPORT for the treatment of hyperhidrosis has not been established. DYSPORT is approved only for intramuscular injection.

5.10 Pre-existing Conditions at the Injection Site

Caution should be exercised when DYSPORT is used where the targeted muscle shows excessive weakness or atrophy.

6 ADVERSE REACTIONS

The following serious adverse reactions are discussed below and elsewhere in labeling:

- Spread of Toxin Effect [ see Warnings and Precautions (5.1)]
- Lack of Interchangeability between Botulinum Toxin Products [ see Warnings and Precautions (5.2)]
- Hypersensitivity Reactions [see Warnings and Precautions (5.3)]
- Dysphagia and Breathing Difficulties [ see Warnings and Precautions (5.4)]
- Facial Anatomy in the Treatment of Glabellar Lines [ see Warnings and Precautions (5.5)]
- Dry Eye with the Treatment of Glabellar Lines [see Warnings and Precautions (5.6)]
- Pre-existing Neuromuscular Disorders [ see Warnings and Precautions (5.7)]
- Human Albumin and Transmission of Viral Diseases [ see Warnings and Precautions (5.8)]
- Intradermal Immune Reaction [ see Warnings and Precautions (5.9)]
- Pre-existing Conditions at the Injection Site [ See Warnings and Precautions (5.10)]

6.1 Clinical Trials Experience

Because clinical trials are conducted under widely varying conditions, adverse reaction rates observed in the clinical trials of a drug cannot be directly compared to rates in the clinical trials of another drug and may not reflect the rates observed in practice.

Cervical Dystonia

The data described below reflect exposure to DYSPORT in 446 cervical dystonia patients in 7 studies. Of these, two studies were randomized, double-blind, single treatment, placebo-controlled studies with subsequent optional open-label treatment in which dose optimization (250 to 1000 Units per treatment) over the course of 5 treatment cycles was allowed [see Clinical Studies (14.1)].

The population was almost entirely Caucasian (99%) with a median age of 51 years (range 18–82 years). Most patients (87%) were less than 65 years of age; 58.4% were women.

Common Adverse Reactions

The most commonly reported adverse reactions (occurring in 5% or more of patients who received 500 Units of DYSPORT in the placebo-controlled clinical trials) in cervical dystonia patients were: muscular weakness, dysphagia, dry mouth, injection site discomfort, fatigue, headache, musculoskeletal pain, dysphonia, injection site pain and eye disorders (consisting of blurred vision, diplopia, and reduced visual acuity and accommodation). Other than injection site reactions, most adverse reactions became noticeable about one week after treatment and lasted several weeks.

The rates of adverse reactions were higher in the combined controlled and open-label experience than in the placebo-controlled trials.
During the clinical studies, two patients (<1%) experienced adverse reactions leading to withdrawal. One patient experienced disturbance in attention, eyelid disorder, feeling abnormal and headache, and one patient experienced dysphagia.

Table 7 compares the incidence of the most frequent adverse reactions from a single treatment cycle of 500 Units of DYSPORT compared to placebo [ see Clinical Studies (14.1)].

Table 7: Most Common Adverse Reactions (≥ 5%) and Greater than Placebo in the Pooled, Double-blind, Placebo-Controlled Phase of Clinical Trials in Patients with Cervical Dystonia
Adverse Reactions | DYSPORT 500 Units (N=173) | Placebo (N=182)
 | % | %
Any Adverse Reaction | 61 | 51
General disorders and administration site conditions
Injection site discomfort | 13 | 8
Fatigue | 12 | 10
Injection site pain | 5 | 4
Musculoskeletal and connective tissue disorders
Muscular weakness | 16 | 4
Musculoskeletal pain | 7 | 3
Gastrointestinal disorders
Dysphagia | 15 | 4
Dry Mouth | 13 | 7
Nervous system disorders
Headache | 11 | 9
Respiratory, thoracic and mediastinal disorders
Dysphonia | 6 | 2
Eye Disorders [The following preferred terms were reported: vision blurred, diplopia, visual acuity reduced, eye pain, eyelid disorder, accommodation disorder, dry eye, eye pruritus.] | 7 | 2

Dose-response relationships for common adverse reactions in a randomized multiple fixed-dose study in which the total dose was divided between two muscles (the sternocleidomastoid and splenius capitis) are shown in Table 8.

Table 8: Common Adverse Reactions by Dose in Fixed-dose Study in Patients with Cervical Dystonia
Adverse Reactions | DYSPORT Dose
Adverse Reactions | 250 Units % | 500 Units % | 1000 Units % | Placebo %
Any Adverse Reaction | 37 | 65 | 83 | 30
Dysphagia | 21 | 29 | 39 | 5
Dry Mouth | 21 | 18 | 39 | 10
Muscular Weakness | 11 | 12 | 56 | 0
Injection Site Discomfort | 5 | 18 | 22 | 10
Dysphonia | 0 | 18 | 28 | 0
Facial Paresis | 5 | 0 | 11 | 0
Eye Disorder [The following preferred terms were reported: vision blurred, diplopia, visual acuity reduced, eye pain, eyelid disorder, accommodation disorder, dry eye, eye pruritus] | 0 | 6 | 17 | 0

Injection Site Reactions

Injection site discomfort and injection site pain were common adverse reactions following DYSPORT administration.

Less Common Adverse Reactions

The following adverse reactions were reported less frequently (<5%).

Breathing Difficulty

Breathing difficulties were reported by approximately 3% of patients following DYSPORT administration and in 1% of placebo patients in clinical trials during the double-blind phase. These consisted mainly of dyspnea. The median time to onset from last dose of DYSPORT was approximately one week, and the median duration was approximately three weeks.

Other adverse reactions with incidences of less than 5% in the DYSPORT 500 Units group in the double-blind phase of clinical trials included dizziness in 3.5% of DYSPORT-treated patients and 1% of placebo-treated patients, and muscle atrophy in 1% of DYSPORT-treated patients and in none of the placebo-treated patients.

Laboratory Findings

Patients treated with DYSPORT exhibited a small increase from baseline (0.23 mol/L) in mean blood glucose relative to placebo-treated patients. This was not clinically significant among patients in the development program but could be a factor in patients whose diabetes is difficult to control.

Electrocardiographic Findings

ECG measurements were only recorded in a limited number of patients in an open-label study without a placebo or active control. This study showed a statistically significant reduction in heart rate compared to baseline, averaging about three beats per minute, observed thirty minutes after injection.

Glabellar Lines

In placebo-controlled clinical trials of DYSPORT, the most common adverse reactions(≥2%) following injection of DYSPORT were nasopharyngitis, headache, injection site pain, injection site reaction, upper respiratory tract infection, eyelid edema, eyelid ptosis, sinusitis, nausea, and blood present in urine.

Table 9 reflects exposure to DYSPORT in 398 patients 19 to 75 years of age who were evaluated in the randomized, placebo-controlled clinical studies that assessed the use of DYSPORT for the temporary improvement in the appearance of glabellar lines [ see Clinical Studies (14.2)]. Adverse reactions of any cause occurred in 48% of the DYSPORT-treated patients and 33% of the placebo-treated patients.

Table 9: Most Common Adverse Reactions with > 1% Incidence in Pooled, Placebo-Controlled Trials for Glabellar Lines
Adverse Reactions by Body System | DYSPORT (N=398) % [Patients who received treatment with placebo and DYSPORT are counted in both treatment columns.] | Placebo (N=496) %
Any Adverse Reaction | 48 | 33
Eye Disorders Eyelid Edema Eyelid Ptosis | 2 2 | 0 <1
Gastrointestinal Disorders Nausea | 2 | 1
General Disorders and Administrative Site Conditions Injection Site Pain Injection Site Reaction | 3 3 | 2 < 1
Infections and Infestations Nasopharyngitis Upper Respiratory Tract Infection Sinusitis | 10 3 2 | 4 2 1
Investigations Blood Present in Urine | 2 | < 1
Nervous System Disorders Headache | 9 | 5

In the clinical trials safety database, where some patients received up to twelve treatments with DYSPORT, adverse reactions were reported for 57% (1425/2491) of patients. The most frequently reported of these adverse reactions were headache, nasopharyngitis, injection site pain, sinusitis, URI, injection site bruising, and injection site reaction (numbness, discomfort, erythema, tenderness, tingling, itching, stinging, warmth, irritation, tightness, swelling).

Adverse reactions that occurred after repeated injections in 2–3% of the population included bronchitis, influenza, pharyngolaryngeal pain, cough, contact dermatitis, injection site swelling, and injection site discomfort.

The incidence of eyelid ptosis did not increase in the long-term safety studies with multiple re-treatments at intervals ≥ three months. The majority of the reports of eyelid ptosis were mild to moderate in severity and resolved over several weeks. [ see Dosage and Administration (2.4)]. ].

Spasticity in Adults

Injection Site Reactions
Injection site reactions (e.g. pain, bruising, hemorrhage, erythema/hematoma etc.) have occurred following administration of DYSPORT in adults treated for spasticity.

Upper Limb Spasticity in Adults

Table 10 lists the adverse reactions that occurred in ≥ 2% of patients in any DYSPORT dose group and more frequent than placebo in double-blind studies evaluating the treatment of upper limb spasticity in adults. The most common adverse reactions (≥ 4%) in any DYSPORT dose group was muscular weakness.

Table 10: Most Common Adverse Reactions Observed in at Least 2% of Patients Treated in Pooled, Double-Blind Trials of Adult Patients with Upper Limb Spasticity Reported More Frequently than with Placebo
Adverse Reaction | DYSPORT |  | Placebo
Adverse Reaction | 500 Units (N=197) % | 1000 Units (N=194) % | (N=279) %
Infections and infestations
Influenza | 1 | 2 | 1
Infection | 1 | 2 | 1
Musculoskeletal and connective tissue disorders
Muscular weakness | 2 | 4 | 1
Pain in extremity | 0 | 2 | 1
Back pain | 1 | 2 | 1
Nervous system disorders
Headache | 1 | 2 | 1
Convulsion | 2 | 2 | 1
Syncope | 1 | 2 | 0
Hypoesthesia | 0 | 2 | <1
Partial seizures | 0 | 2 | 0
General disorders and administration site conditions
Fatigue | 2 | 2 | 0
Asthenia | 2 | 1 | <1
Injury, poisoning and procedural complications
Fall | 2 | 3 | 2
Injury | 2 | 2 | 1
Contusion | 1 | 2 | <1
Gastrointestinal disorders
Diarrhea | 1 | 2 | <1
Constipation | 0 | 2 | 1
Investigation
Blood triglycerides increased | 2 | 1 | 0
Respiratory, thoracic and mediastinal disorders
Cough | 1 | 2 | 1
Vascular disorders
Hypertension | 1 | 2 | <1
Psychiatric disorders
Depression | 2 | 3 | 1

Less Common Adverse Reactions
In a pooled analysis of clinical studies, adverse reactions with an incidence of less than 2% reported in DYSPORT treatment groups included dysphagia 0.5%, gait disturbance 0.5%, hypertonia 0.5%, and sensation of heaviness 0.3%.

Lower Limb Spasticity in Adults

The data described below reflect exposure to DYSPORT in 255 adults with lower limb spasticity. Of this population, 89% were Caucasian, 66% male, and the median age was 55 years (range 23-77 years). Table 11 lists the adverse reactions that occurred in ≥ 2% of patients in any DYSPORT dose group and more frequent than placebo in the double-blind study evaluating the treatment of lower limb spasticity in adults. The most common of these adverse reactions (≥ 5%) in any DYSPORT dose group were falls, muscular weakness, and pain in extremity.

Table 11: Adverse Reactions Observed in at Least 2% of Patients Treated in the Double-Blind Trial of Adults with Lower Limb Spasticity and Reported More Frequently than with Placebo
Adverse Reactions | Dysport 1000 U (N = 127) % | Dysport 1500 U (N = 128) % | Placebo (N = 130) %
Musculoskeletal and connective tissue disorders Muscular weakness Pain in extremity Arthralgia | 2 6 4 | 7 6 2 | 3 2 1
Injury, poisoning and procedural complications Fall | 9 | 6 | 3
Nervous system disorders Headache | 0 | 3 | 1
Infections and infestations Upper respiratory tract infection | 2 | 1 | 1
General disorders and administration site conditions Fatigue Influenza-like illness Edema peripheral | 1 2 2 | 4 0 0 | 0 0 0
Investigations Alanine aminotransferase increase | 2 | 0 | 1
Gastrointestinal disorders Constipation | 0 | 2 | 1
Psychiatric disorders Depression Insomnia | 2 0 | 3 2 | 0 0

In the efficacy and safety studies of DYSPORT for the treatment of lower limb spasticity in adults, muscular weakness was reported more frequently in women (10%) treated with 1500 units of DYSPORT compared to men (5%). Falls were reported more frequently in patients 65 years of age and over. [see Use in Specific Populations (8.5)]

Upper Limb Spasticity in Pediatric Patients

Table 12 reflects exposure to DYSPORT in 210 patients, 2 to 17 years of age, who were evaluated in a double blind, active-controlled, multicenter study in patients treated for upper limb spasticity [see Clinical Studies (14.4)].The most commonly observed adverse reactions (≥10% of patients) were: upper respiratory tract infection and pharyngitis.

Table 12: Adverse Reactions Observed in ≥ 3% of Patients Treated in the Double-Blind Study of Pediatric Patients with Upper Limb Spasticity and Reported More Frequently than Control Group
Adverse Reactions | Dysport 2 Units/kg^1 (N=70) % | Dysport 8 Units/kg (N=70) % | Dysport 16 Units/kg (N=70) %
Infections and infestations Upper respiratory tract infection Influenza Pharyngitis^2 | 7 1 9 | 9 1 6 | 11 3 10
Gastrointestinal disorders Nausea | 0 | 3 | 1
Musculoskeletal and connective tissue diorders Muscular weakness | 1 | 4 | 6
Nervous system disorders Headache Epilepsy | 0 1 | 6 0 | 3 4

1 Low dose active comparator arm
2 Includes pharyngitis, pharyngitis streptococcal, pharyngotosilitis

Additional adverse reactions occurring below 3% and considered to be drug related include: myalgia, pain in extremity, fatigue, influenza-like illness, injection site eczema, injection site bruising, injection site rash, injection site pain, and injection site swelling.

Lower Limb Spasticity in Pediatric Patients
Table 13 reflects exposure to DYSPORT in 160 patients, 2 to 17 years of age, who were evaluated in the randomized, placebo-controlled clinical study that assessed the use of DYSPORT for the treatment of unilateral or bilateral lower limb spasticity in pediatric cerebral palsy patients [ see Clinical Studies (14.4)]. The most commonly observed adverse reactions (≥ 10% of patients) are: upper respiratory tract infection, nasopharyngitis, influenza, pharyngitis, cough and pryrexia.

Table 13: Adverse Reactions Observed in ≥ 4% of Patients Treated in the Double-Blind Trial of Pediatric Patients with Lower Limb Spasticity and Reported More Frequently than with Placebo
Adverse Reactions |  | Unilteral |  | Bilateral
Adverse Reactions | Dysport 10 units/kg (N=43) % | Dysport 15 units/kg (N=50) % | Dysport 20 units/kg (N=37) % | Dysport 30 units/kg (N=30) % | Placebo (N=79) %
Infections and Infestations
Nasopharyngitis | 9 | 12 | 16 | 10 | 5
Bronchitis | 0 | 0 | 8 | 7 | 3
Respiratory, thoracic and mediastinal disorders
Cough | 7 | 6 | 14 | 10 | 6
General disorders and administration site conditions
Pyrexia | 7 | 12 | 8 | 7 | 5
Musculoskeletal and connective tissue disorders
Pain in extremity | 0 | 2 | 5 | 7 | 5
Nervous system disorders
Convulsion/Epilepsy | 7 | 4 | 0 | 7 | 0

6.2 Immunogenicity

As with all therapeutic proteins, there is a potential for immunogenicity.

The incidence of antibody formation is highly dependent on the sensitivity and specificity of the assay. In addition, the observed incidence of antibody positivity in an assay may be influenced by several factors including assay methodology, sample handling, timing of sample collection, concomitant medications, and underlying disease. For these reasons, comparison of the incidence of antibodies across products in this class may be misleading.

Cervical Dystonia

About 3% of subjects developed antibodies (binding or neutralizing) over time with DYSPORT treatment.

Glabellar Lines

Testing for antibodies to DYSPORT was performed for 1554 subjects who had up to nine cycles of treatment. Two subjects (0.13%) tested positive for binding antibodies at baseline. Three additional subjects tested positive for binding antibodies after receiving DYSPORT treatment. None of the subjects tested positive for neutralizing antibodies.

Spasticity in Adults
Upper Limb Spasticity

From 230 subjects treated with DYSPORT and tested for the presence of binding antibodies, 5 subjects were positive at baseline and 17 developed antibodies after treatment. Among those 17 subjects, 10 subjects developed neutralizing antibodies. An additional 51 subjects from a separate repeat-dose study were tested for the presence of neutralizing antibodies only. None of the subjects tested positive.

In total, from the 281 subjects treated in the long-term studies and tested for the presence of neutralizing antibodies, 3.6% developed neutralizing antibodies after treatment. In the presence of binding and neutralizing antibodies to DYSPORT some patients continue to experience clinical benefit.

Lower Limb Spasticity

From 367 subjects treated with DYSPORT and tested for the presence of binding antibodies, 4 subjects were positive at baseline and 2 developed binding antibodies after treatment. No subjects developed neutralizing antibodies. An additional 85 subjects from two separate studies were tested for the presence of neutralizing antibodies only. One subject tested positive for the presence of neutralizing antibodies.

In total, from the 452 subjects treated in with DYSORT and tested for the presence of neutralizing antibodies, 0.2% developed neutralizing antibodies after treatment.

Spasticity in Pediatric Patients 2 Years of Age or Older

Upper Limb Spasticity
From 178 subjects treated with DYSPORT for up to 4 treatment cycles and tested for the presence of binding antibodies at baseline and end of study, 7 subjects previously receiving botulinum toxin injections had binding antibodies after treatment. Among those 7 subjects, 4 subjects (2.3%) developed neutralizing antibodies when tested in the mice bioassay. In the presence of binding and/or neutralizing antibodies to DYSPORT some patients continue to experience clinical benefit.

Lower Limb Spasticity
From 226 subjects treated with DYSPORT and tested for the presence of binding antibodies, 5 subjects previously receiving botulinum toxins were positive at baseline and 9 patients developed binding antibodies after injections. Among those 9 subjects, 3 subjects developed neutralizing antibodies, while one subject developed neutralizing antibodies from the 5 subjects testing positive for binding antibodies at baseline who previously received botulinum toxin injections.

From a separate repeat-dose study, 203 subjects were tested for the presence of neutralizing antibodies. Two subjects were positive for neutralizing antibodies at baseline and 5 subjects developed neutralizing antibodies after treatments. In total, from the 429 patients tested for the presence of neutralizing antibodies, 2.1% developed neutralizing antibodies after treatment. In the presence of binding and neutralizing antibodies to DYSPORT, some patients continued to experience clinical benefit.

6.3 Postmarketing Experience

Because adverse reactions are reported voluntarily from a population of uncertain size, it is not always possible to reliably estimate their frequency or establish a causal relationship to drug exposure.
The following adverse reactions have been identified during post-approval use of DYSPORT: vertigo, photophobia, influenza-like illness, amyotrophy, muscle atrophy, burning sensation, facial paresis, hypoesthesia, erythema, dry eye, and excessive granulation tissue. Hypersensitivity reactions including anaphylaxis have been reported.

7 DRUG INTERACTIONS

7.1 Aminoglycosides and Other Agents Interfering with Neuromuscular Transmission

Co-administration of DYSPORT and aminoglycosides or other agents interfering with neuromuscular transmission (e.g., curare-like agents) should only be performed with caution because the effect of the botulinum toxin may be potentiated. If co-administered, observe the patient closely.

7.2 Anticholinergic Drugs

Use of anticholinergic drugs after administration of DYSPORT may potentiate systemic anticholinergic effects such as blurred vision.

7.3 Other Botulinum Neurotoxin Products

The effect of administering botulinum neurotoxin products including DYSPORT, at the same time or within several months of each other is unknown. Excessive weakness may be exacerbated by another administration of botulinum toxin prior to the resolution of the effects of a previously administered botulinum toxin.

7.4 Muscle Relaxants

Excessive weakness may also be exaggerated by administration of a muscle relaxant before or after administration of DYSPORT.

8 USE IN SPECIFIC POPULATIONS

8.1 Pregnancy

TERATOGENIC EFFECTS

Risk Summary
There are no adequate and well-controlled clinical studies with DYSPORT in pregnant women.
DYSPORT should only be used during pregnancy if the potential benefit justifies the potential risk to the fetus.
DYSPORT produced embryo-fetal toxicity in relation to maternal toxicity when given to pregnant rats and rabbits at doses lower than or similar to the maximum recommended human dose (MRHD) of 1000 Units on a body weight (Units/kg) basis (see Data).
In the U.S. general population, the estimated background risk of major birth defects and miscarriage in clinically recognized pregnancies is 2-4% and 15-20%, respectively. The background risk of major birth defects and miscarriage for the indicated population is unknown.

Data
Animal Data
In a study in which pregnant rats received daily intramuscular injections of DYSPORT (2.2, 6.6, or 22 Units/kg on gestation days 6 through 17 or intermittently 44 Units/kg on gestation days 6 and 12 only) during organogenesis, increased early embryonic death was observed with both schedules at the highest tested doses (22 and 44 Units/kg), which were associated with maternal toxicity. The no-effect dose for embryo-fetal developmental toxicity was 2.2 Units/kg (less than maximum recommended human [MRHD] on a body weight basis).

In a study in which pregnant rabbits received daily intramuscular injections of DYSPORT® (0.3, 3.3 or 6.7 Units/kg) on gestation days 6 through 19 or intermittently (13.3 Units/kg on gestation days 6 and 13 only) during organogenesis, no embryofetal data were available at the highest dose administered daily (6.7 Units/kg) because of premature death in all does at that dose. At the lower daily doses or with intermittent dosing, no adverse developmental effects were observed. All dosed for which data were available are less than the MRHD on a body weight basis.

In a study in which pregnant rats received 6 weekly intramuscular injections of DYSPORT (4.4, 11.1, 22.2, or 44 Units/kg) beginning on day 6 of gestation and continuing through parturition to weaning, an increase in stillbirths was observed at the highest dose tested, which was maternally toxic. The no-effect dose for pre- and post-natal development toxicity was 22.2 Units/kg (similar to the MRHD).

8.2 Lactation

Risk Summary
There are no data on the presence of DYSPORT in human or animal milk, the effects on the breastfed infant, or the effects on milk production.

The development and health benefits of breastfeeding should be considered along with the mother's clinical need for DYSPORT and any potential adverse effects on the breastfed infant from DYSPORT or from the underlying maternal condition.

8.3 Females and Males of Reproductive Potential

Infertility

In rats, DYSPORT produced adverse effects on mating behavior and fertility [ see Nonclinical Toxicology (13.1)].

8.4 Pediatric Use

Cervical Dystonia

Safety and effectiveness in pediatric patients have not been established [see Boxed Warning and Warnings and Precautions (5.2)].

Glabellar Lines

DYSPORT is not recommended for use in pediatric patients less than 18 years of age.

Spasticity

Safety and effectiveness have been established in pediatric patients 2 years of age and older [see Warnings and Precautions (5.1), Adverse Reactions (6.1), and Clinical Studies (14.4)]. The safety and effectiveness of DYSPORT have been established by evidence from adequate and well-controlled studies of DYSPORT in patients 2 years of age and older with upper and lower limb spasticity. The safety and effectiveness of DYSPORT injected into proximal muscles of the lower limb for the treatment of spasticity in pediatric patients has not been established [see Boxed Warning, Warnings and Precautions (5.2), and Adverse Reactions (6.1)].
Safety and effectiveness in pediatric .below the age of 2 years have not been established [see Boxed Warning and Warnings and Precautions (5.2)].

Juvenile Animal Data

In a study in which juvenile rats received a single intramuscular injection of DYSPORT (1, 3 or 10 Units/animal) on postnatal day 21, decreased growth and bone length (injected and contralateral limbs), delayed sexual maturation, and decreased fertility were observed at the highest dose tested, which was associated with excessive toxicity during the first week after dosing.

In a study in which juvenile rats received weekly intramuscular injections of DYSPORT (0.1, 0.3, or 1.0 Units/animal) from postnatal day 21 to 13 weeks of age, decreases in bone mineral content in the injected limb, associated with atrophy of injected and adjacent muscles, were observed at the highest dose tested. No adverse effects were observed on neurobehavioral development. However, dose levels were not adjusted for growth of the pups. On a body weight basis, the doses at the end of the dosing period were approximately 15% of those at initiation of dosing. Therefore, the effects of DYSPORT throughout postnatal development were not adequately evaluated.

8.5 Geriatric Use

Cervical Dystonia

There were insufficient numbers of patients aged 65 years and over in the clinical studies to determine whether they respond differently than younger patients. In general, elderly patients should be observed to evaluate their tolerability of DYSPORT, due to the greater frequency of concomitant disease and other drug therapy [ see Dosage and Administration (2.3)].

Glabellar Lines

Of the total number of subjects in the placebo-controlled clinical studies of DYSPORT, 8 (1%) were 65 years and over. Efficacy was not observed in subjects aged 65 years and over [ see Clinical Studies (14.2)]. For the entire safety database of geriatric subjects, although there was no increase in the incidence of eyelid ptosis, geriatric subjects did have an increase in the number of ocular adverse reactions compared to younger subjects (11% vs. 5%) [ see Dosage and Administration (2.4)].

Adult Spasticity
Upper Limb Spasticity

Of the total number of subjects in placebo-controlled clinical studies of DYSPORT, 30 percent were aged 65 years and over, while 8 percent were aged 75 years and over. No overall differences in safety or effectiveness were observed between these subjects and younger subjects. Other reported clinical experience has not identified differences in responses between the elderly and younger patients, but greater sensitivity of some older individuals can not be ruled out.

Lower Limb Spasticity

Of the total number of subjects in placebo controlled clinical studies of DYSPORT, 18% (n=115) were 65 and over, while 3% (n=20) were 75 and over. Subjects aged 65 years and over who were treated with DYSPORT reported a greater percentage of adverse reactions as compared to younger subjects (46% versus 39%). Fall and asthenia were observed with greater frequency in older subjects, as compared to those younger (10% versus 6% and 4% versus 2%, respectively).

8.6 Ethnic Groups

Exploratory analyses in trials for glabellar lines in African-American subjects with Fitzpatrick skin types IV, V, or VI and in Hispanic subjects suggested that response rates at Day 30 were comparable to and no worse than the overall population.

10 OVERDOSAGE

Excessive doses of DYSPORT may be expected to produce neuromuscular weakness with a variety of symptoms. Respiratory support may be required where excessive doses cause paralysis of respiratory muscles. In the event of overdose, the patient should be medically monitored for symptoms of excessive muscle weakness or muscle paralysis [ see Boxed Warning and Warnings and Precautions (5.2)]. Symptomatic treatment may be necessary.

Symptoms of overdose are likely not to be present immediately following injection. Should accidental injection or oral ingestion occur, the person should be medically supervised for several weeks for signs and symptoms of excessive muscle weakness or paralysis.

There is no significant information regarding overdose from clinical studies.

In the event of overdose, antitoxin raised against botulinum toxin is available from the Centers for Disease Control and Prevention (CDC) in Atlanta, GA. However, the antitoxin will not reverse any botulinum toxin-induced effects already apparent by the time of antitoxin administration. In the event of suspected or actual cases of botulinum toxin poisoning, please contact your local or state Health Department to process a request for antitoxin through the CDC. If you do not receive a response within 30 minutes, please contact the CDC directly at 770-488-7100. More information can be obtained at https://www.cdc.gov/laboratory/drugservice/index.html.

11 DESCRIPTION

Botulinum toxin type A, the active ingredient in DYSPORT, is a purified neurotoxin type A complex produced by fermentation of the bacterium Clostridium botulinumtype A, Hall Strain. It is purified from the culture supernatant by a series of precipitation, dialysis, and chromatography steps. The neurotoxin complex is composed of the neurotoxin, hemagglutinin proteins and non-toxin non-hemagglutinin protein.

DYSPORT® (abobotulinumtoxinA) for injection is a sterile, lyophilized powder supplied in a single-dose vial for reconstitution intended for intramuscular injection. Each vial contains 300 Units or 500 Units of lyophilized abobotulinumtoxinA, human serum albumin (125 mcg) and lactose (2.5 mg). DYSPORT may contain trace amounts of cow's milk proteins [ see Contraindications (4) and Warnings and Precautions (5.3)]. ].

The primary release procedure for DYSPORT uses a cell-based potency assay to determine the potency relative to a reference standard. The assay and reference material are specific to DYSPORT. One unit of DYSPORT corresponds to the calculated median lethal intraperitoneal dose (LD50) in mice. Due to specific details of the assay system, such as vehicle, dilution scheme and laboratory protocols, Units of biological activity of DYSPORT cannot be converted into Units of any other botulinum toxin or any toxin assessed with any other specific assay method.

12 CLINICAL PHARMACOLOGY

12.1 Mechanism of Action

DYSPORT inhibits release of the neurotransmitter, acetylcholine, from peripheral cholinergic nerve endings. Toxin activity occurs in the following sequence: Toxin heavy chain mediated binding to specific surface receptors on nerve endings, internalization of the toxin by receptor mediated endocytosis, pH-induced translocation of the toxin light chain to the cell cytosol and cleavage of SNAP25 leading to intracellular blockage of neurotransmitter exocytosis into the neuromuscular junction. This accounts for the therapeutic utility of the toxin in diseases characterized by excessive efferent activity in motor nerves.

Recovery of transmission occurs gradually as the neuromuscular junction recovers from SNAP25 cleavage and as new nerve endings are formed.

12.2 Pharmacodynamics

The primary pharmacodynamic effect of DYSPORT is due to chemical denervation of the treated muscle resulting in a measurable decrease of the compound muscle action potential, causing a localized reduction of muscle activity.

12.3 Pharmacokinetics

Using currently available analytical technology, it is not possible to detect DYSPORT in the peripheral blood following intramuscular injection at the recommended doses.

13 NONCLINICAL TOXICOLOGY

13.1 Carcinogenesis, Mutagenesis, Impairment of Fertility

Carcinogenesis

Studies to evaluate the carcinogenic potential of DYSPORT have not been conducted.

Mutagenesis

Genotoxicity studies have not been conducted for DYSPORT.

Impairment of Fertility

In a fertility and early embryonic development study in rats in which either males (2.9, 7.2, 14.5 or 29 Units/kg) or females (7.4, 19.7, 39.4 or 78.8 Units/kg) received weekly intramuscular injections prior to and after mating, dose-related increases in pre-implantation loss and reduced numbers of corpora lutea were noted in treated females. Failure to mate was observed in males that received the high dose. The no-effect dose for effects on fertility was 7.4 Units/kg in females and 14.5 Units/kg in males (approximately one-half and equal to, respectively, the maximum recommended human dose of 1000 Units on a body weight basis).

14 CLINICAL STUDIES

14.1 Cervical Dystonia

The efficacy of DYSPORT was evaluated in two randomized, double-blind, placebo-controlled, single-dose, parallel-group studies in treatment-naive cervical dystonia patients. The principal analyses from these trials provide the primary demonstration of efficacy involving 252 patients (121 on DYSPORT, 131 on placebo) with 36% male and 64% female. Ninety-nine percent of the patients were Caucasian.

In both placebo-controlled studies (Study 1 and Study 2), a dose of 500 Units of DYSPORT was given by intramuscular injection divided among two to four affected muscles. These studies were followed by long-term open-label extensions that allowed titration in 250 Unit steps to doses in a range of 250 to 1000 Units, after the initial dose of 500 Units. In the extension studies, re-treatment was determined by clinical need after a minimum of 12 weeks. The median time to re-treatment was 14 weeks and 18 weeks for the 75thpercentile.

The primary assessment of efficacy was based on the total Toronto Western Spasmodic Torticollis Rating Scale (TWSTRS) change from baseline at Week 4 for both studies. The scale evaluates the severity of dystonia, patient-perceived disability from dystonia, and pain. The adjusted mean change from baseline in the TWSTRS total score was statistically significantly greater for the DYSPORT group than the placebo group at Weeks 4 in both studies (see Table 14) .

Table 14: TWSTRS Total Score Efficacy Outcome from the Phase 3 Cervical Dystonia Studies Intent to Treat Population
 | Study 1 |  | Study 2
 | DYSPORT 500 Units N=55 | Placebo N=61 | DYSPORT 500 Units N=37 | Placebo N=43
Baseline (week 0) Mean (SD) | 43.8 (8.0) | 45.8 (8.9) | 45.1 (8.7) | 46.2 (9.4)
Week 4 Mean (SD) Change from Baseline [Change from baseline is expressed as adjusted least square mean (SE)] | 30.0 (12.7) -15.6 (2.0) | 40.2 (11.8) -6.7 (2.) | 35.2 (13.8) -9.6 (2.0) | 42.4 (12.2) -3.7 (1.8)
treatment difference 95% confidence interval | -8.9 [Significant at p-value < 0.05] [-12.9 to -4.7] |  | -5.9 [-10.6 to -1.3]
Week 8 Mean (SD) Change from Baseline | 29.2 (11.0) -14.7 (2.0) | 39.6 (13.5) -5.9 (2.0)
treatment difference 95% confidence interval | -8.8 [-12.9 to -4.7]

Analyses by gender, weight, geographic region, underlying pain, cervical dystonia severity at baseline and history of treatment with botulinum toxin did not show any meaningful differences between groups.

Table 15 indicates the average DYSPORT dose, and percentage of total dose, injected into specific muscles in the pivotal clinical trials.

Table 15: DYSPORT 500 Units starting dose (units and % of the total dose) by Unilateral Muscle Injected During Double-blind Pivotal Phase 3 studies 2 and 1 Combined
Number of patients injected per muscle [Total number of patients in combined studies 2 and 1 who received initial treatment = 121.] |  | DYSPORT Dose Injected |  | Percentage of the total DYSPORT Dose Injected
 |  | Median [DYSPORT Units] (min, max) | 75th percentile [DYSPORT Units] | Median [%] (min, max) | 75th percentile [%]
Sternocleidomastoid | 90 | 125 Units (50, 350) | 150 Units | 26.5% (10, 70) | 30.0%
Splenius capitis | 85 | 200 Units (75, 450) | 250 Units | 40.0% (15, 90) | 50.0%
Trapezius | 50 | 102.6 Units (50, 300) | 150 Units | 20.6% (10, 60) | 30.0%
Levator scapulae | 35 | 105.3 Units (50, 200) | 125 Units | 21.1% (10, 40) | 25.0%
Scalenus (medius and anterior) | 26 | 115.5 Units (50, 300) | 150 Units | 23.1% (10,60) | 30.0%
Semispinalis capitis | 21 | 131.6 Units (50, 250) | 175 Units | 29.4% (10, 50) | 35.0%
Longissimus | 3 | 150 Units (100, 200) | 200 Units | 30.0% (20, 40) | 40.0%

14.2 Glabellar Lines

Three double-blind, randomized, placebo-controlled, clinical studies evaluated the efficacy of DYSPORT for use in the temporary improvement of the appearance of moderate to severe glabellar lines. These three studies enrolled healthy adults (ages 19-75) with glabellar lines of at least moderate severity at maximum frown. Subjects were excluded if they had marked ptosis, deep dermal scarring, or a substantial inability to lessen glabellar lines, even by physically spreading them apart. The subjects in these studies received either DYSPORT or placebo. The total dose was delivered in equally divided aliquots to specified injection sites (see Figure 1).

Investigators and subjects assessed efficacy at maximum frown by using a 4-point scale (none, mild, moderate, severe).

Overall treatment success was defined as post-treatment glabellar line severity of none or mild with at least 2 grade improvement from Baseline for the combined investigator and subject assessments (composite assessment) on Day 30 (see Table 16). Additional endpoints for each of the studies were post-treatment glabellar line severity of none or mild with at least a 1 grade improvement from Baseline for the separate investigator and subject assessments on Day 30.

After completion of the randomized studies, subjects were offered participation in a two-year, open-label re-treatment study to assess the safety of multiple treatments.

Table 16: Treatment Success at Day 30 (None or Mild with at least a 2 Grade Improvement from Baseline at Maximum Frown for the combined Investigator and Subject Assessments (Composite))
 | 2 Grade Improvement
Study | DYSPORT n/N (%) | Placebo n/N (%)
GL-1 | 58/105 (55%) | 0/53 (0%)
GL-2 | 37/71 (52%) | 0/71 (0%)
GL-3 | 120/200 (60%) | 0/100 (0%)

Treatment with DYSPORT reduced the severity of glabellar lines for up to four months.

Study GL-1

Study GL-1 was a single-dose, double-blind, multicenter, randomized, placebo-controlled study in which 158 previously untreated subjects received either placebo or 50 Units of DYSPORT, administered in five aliquots of 10 Units (see Figure 1). Subjects were followed for 180 days. The mean age was 43 years; most of the subjects were women (85%), and predominantly Caucasian (49%) or Hispanic (47%). At Day 30, 55% of DYSPORT-treated subjects achieved treatment success: a composite 2 grade improvement of glabellar line severity at maximum frown (Table 16).

In study GL-1, the reduction of glabellar line severity at maximum frown was greater at Day 30 in the DYSPORT group compared to the placebo group as assessed by both Investigators and subjects (Table 17).

Table 17: GL-1: Investigators' and Subjects' Assessment of Glabellar Line Severity at Maximum Frown Using a 4-point Scale (% and Number of Subjects with Severity of None or Mild)
 | Investigators' Assessment |  | Subjects' Assessment
Day | DYSPORT N=105 | Placebo N=53 | DYSPORT N=105 | Placebo N=53
14 | 90% 95 | 17% 9 | 77% 81 | 9% 5
30 | 88% 92 | 4% 2 | 74% 78 | 9% 5
60 | 64% 67 | 2% 1 | 60% 63 | 6% 3
90 | 43% 45 | 6% 3 | 36% 38 | 6% 3
120 | 23% 24 | 4% 2 | 19% 20 | 6% 3
150 | 9% 9 | 2% 1 | 8% 8 | 4% 2
180 | 6% 6 | 0% 0 | 7% 7 | 8% 4

Study GL-2

Study GL-2 was a repeat-dose, double-blind, multicenter, placebo-controlled, randomized study. The study was initiated with two or three open-label treatment cycles of 50 Units of DYSPORT administered in five aliquots of 10 Units DYSPORT (see Figure 1). After the open-label treatments, subjects were randomized to receive either placebo or 50 Units of DYSPORT. Subjects could have received up to four treatments through the course of the study. Efficacy was assessed in the final randomized treatment cycle. The study enrolled 311 subjects into the first treatment cycle and 142 subjects were randomized into the final treatment cycle. Overall, the mean age was 47 years; most of the subjects were women (86%) and predominantly Caucasian (80%).

At Day 30, 52% of DYSPORT -treated subjects achieved treatment success: a composite 2 grade improvement of glabellar line severity at maximum frown (see Table 16).

The proportion of responders in the final treatment cycle was comparable to the proportion of responders in all prior treatment cycles.

After the final repeat treatment with DYSPORT, the reduction of glabellar line severity at maximum frown was greater at Day 30 in the DYSPORT group compared to the placebo group as assessed by both Investigators and subjects (see Table 18).

Table 18: GL-2 Investigators' and Subjects' Assessments of Glabellar Line Severity at Maximum Frown Using a 4-point Scale (% and Number of Subjects with Severity of None or Mild)
 | Investigators' Assessment |  | Subjects' Assessment
Day | DYSPORT N=71 | Placebo N=71 | DYSPORT N=71 | Placebo N=71
30 | 85% 60 | 4% 3 | 79% 56 | 1% 1

Study GL-3

Study GL-3 was a single-dose, double-blind, multicenter, randomized, placebo-controlled study in which 300 previously untreated subjects received either placebo or 50 Units of DYSPORT, administered in five aliquots of 10 Units (see Figure 1). Subjects were followed for 150 days. The mean age was 44 years; most of the subjects were women (87%), and predominantly Caucasian (75%) or Hispanic (18%).

At Day 30, 60% of DYSPORT-treated subjects achieved treatment success: a composite 2 grade improvement of glabellar line severity at maximum frown (see Table 16).

In study GL-3, the reduction of glabellar line severity at maximum frown was greater at Day 30 in the DYSPORT group compared to the placebo group as assessed by both Investigators and subjects (see Table 19).

Table 19: GL-3 Investigators' and Subjects' Assessment of Glabellar Line Severity at Maximum Frown Using a 4-point Scale (% and Number of Subjects with Severity of None or Mild)
 | Investigators' Assessment |  | Subjects' Assessment
Day | DYSPORT N=200 | Placebo N=100 | DYSPORT N=200 | Placebo N=100
14 | 83% 166 | 5% 5 | 83% 165 | 2% 2
30 | 86% 171 | 0% 0 | 82% 163 | 2% 2
60 | 75% 150 | 1% 1 | 65% 130 | 4% 4
90 | 51% 102 | 1% 1 | 46% 91 | 2% 2
120 | 29% 58 | 1% 1 | 31% 61 | 3% 3
150 | 16% 32 | 1% 1 | 16% 31 | 3% 3

Geriatric Subjects

In GL1, GL2, and GL3, there were 8 subjects aged 65 and older who were randomized to DYSPORT 50 Units in 5 equal aliquots of 10 Units (4) or placebo (4). None of the geriatric DYSPORT subjects were a treatment success at maximum frown at Day 30.

14.3 Spasticity in Adults

Upper Limb Spasticity
The efficacy and safety of DYSPORT for the treatment of upper limb spasticity in adults was evaluated in a randomized, multicenter, double-blind, placebo-controlled study that included 238 patients (159 DYSPORT and 79 placebo) with upper limb spasticity (Modified Ashworth Scale (MAS) score ≥2 in the primary targeted muscle group for toxin-naive patients or MAS score ≥3 in the primary targeted muscle group for toxin non-naive patients at least 4 months after the last botulinum toxin injection, of any serotype) who were at least 6 months post-stroke or post-traumatic brain injury. The median age of the patients in this study was 55 years (range 18 to 78 years), 64% were male, and 86% were Caucasian.

DYSPORT 500 Units (N=80), DYSPORT 1000 Units (N=79), or placebo (N=79) was injected intramuscularly into the affected upper limb muscles. After injection of the primary targeted muscle groups (PTMG), the remainder of the dose was injected into at least two additional upper limb muscles determined by the patient's individual presentation. Table 20 provides the mean and range of DYSPORT doses injected and the number of injections into specific muscles of the upper limb.

Table 20: DYSPORT Dose Injected and Number of Injections per Muscle in Adults with Upper Limb Spasticity
Muscle | DYSPORT Treatment Group | Number of Patients | Mean DYSPORT Units injected (Min, Max) | Number of Injection Sites Median [Q1 ; Q3]
Flexor digitorum profundus (FDP)* | 500 U 1000 U | 54 65 | 93.5 Units (50 to 100) 195.5 Units (100 to 300) | 1, [1 ; 2] 2, [1 ; 2]
Flexor digitorum superficialis (FDS)* | 500 U 1000 U | 63 73 | 95.4 Units (50 to 100) 196.8 Units (100 to 300) | 2, [1 ; 2] 2, [1 ; 2]
Flexor carpi radialis (FCR)* | 500 U 1000 U | 57 57 | 92.2 Units (25 to 100) 178.1 Units (80 to 300) | 1, [1 ; 2] 1, [1 ; 2]
Flexor carpi ulnaris (FCU)* | 500 U 1000 U | 47 49 | 89.9 Units (25 to 180) 171.2 Units (80 to 200) | 1, [1 ; 2] 1, [1 ; 2]
Brachialis* | 500 U 1000 U | 60 43 | 148.5 Units (50 to 200) 321.4 Units (100 to 300) | 2, [1 ; 2] 2, [1 ; 2]
Brachioradialis* | 500 U 1000 U | 42 28 | 88.3 Units (50 to 200) 172.1Units (50 to 200) | 1, [1 ; 2] 1, [1 ; 2]
Biceps Brachii (BB) | 500 U 1000 U | 28 19 | 106.4 Units (50 to 200) 207.4 Units (100 to 400) | 2, [1 ; 2] 2, [1 ; 2]
Pronator Teres | 500 U 1000 U | 14 30 | 81.8 Units (45 to 200) 157.3 Units (80 to 200) | 1, [1 ; 2] 1, [1 ; 2]
*Primary Targeted Muscle Group

The co-primary efficacy variables were muscle tone assessed by the MAS at the primary targeted muscle group at week 4 and the Physician Global Assessment (PGA; ranges from -4 = marked worse to +4 = marked improved) at week 4 (see Table 21).

Table 21: Primary Endpoints (PTMG MAS and PGA) and MAS by Muscle Group at Week 4 in Adults with Upper Limb Spasticity
 | Placebo (N=79) | DYSPORT
 | Placebo (N=79) | (500 units) (N=80) | (1000 units) (N=79)
LS Mean Change from Baseline in PTMG Muscle Tone on the MAS | -0.3 | -1.2* | -1.4*
LS Mean PGA of Response to Treatment | 0.7 | 1.4* | 1.8*
LS Mean Change from Baseline in Wrist Flexor Muscle Tone on the MAS | -0.3 (n=54) | -1.4 (n=57) | -1.6 (n-58)
LS Mean Change from Baseline in Finger Flexor Muscle Tone on the MAS | -0.3 (n=70) | -0.9 (n=66) | -1.2 (n=73)
LS Mean Change from Baseline in Elbow Flexor Muscle Tone on the MAS | -0.3 (n=56) | -1.0 (n=61) | -1.2 (n=48)
LS= Least Square
*p≤0.05

Lower Limb Spasticity
The efficacy of DYSPORT for the treatment of lower limb spasticity was evaluated in a randomized, multicenter, double-blind, placebo-controlled study that included 381 patients (253 DYSPORT and 128 placebo). Patients had lower limb spasticity (Modified Ashworth Scale (MAS) score ≥2 in the affected ankle joint for toxin-naive patients, or MAS score ≥3 in the affected ankle joint for toxin non-naive patients) and were at least 6 months post-stroke or post-traumatic brain injury.

Table 22 provides the median DYSPORT doses injected and the number of injections into specific muscles of the lower limb as reported in the double-blind study. In the study, the gastrocnemius and soleus muscles, and at least one additional lower limb muscle were injected, according to the clinical presentation.

Table 22: DYSPORT Dose Injected and Number of Injections per Muscle in the Lower Limb - Median for the 1000 Unit and 1500 Unit Dose Groups
Injected Muscle | DYSPORT Units Injected | Number of Injection Sites
Gastrocnemius Lateral Medial | 100 Units to 150 Units | 1
Gastrocnemius Lateral Medial | 100 Units to 150 Units | 1
Soleus | 333 Units to 500 Units | 3
Tibialis posterior | 200 Units to 300 Units | 2
Flexor digitorum longus | 133 Units to 200 Units | 1 to 2
Flexor hallucis longus | 67 Units to 200 Units | 1

The primary efficacy variable was muscle tone assessed by the MAS at the ankle joint at week 4. The first secondary endpoint was the Physician Global Assessment at week 4 (see Table 23).

Table 23: Primary Endpoint Change in MAS and the First Secondary Endpoint PGA at Week 4 in Adults with Lower Limb Spasticity
LS Mean Change from Baseline on the Modified Ashworth Scale | DYSPORT 1000 Units (N=125) | DYSPORT 1500 Units (N=128) | Placebo (N=128)
Week 4 | -0.6 | -0.8 [P‹0.05] | -0.5
LS Mean Physician Global Assessment Score Investigator
Week 4 | 0.9 | 0.9 | 0.7

14.4 Spasticity in Pediatric Patients

Upper Limb Spasticity in Pediatric Patients
The efficacy of DYSPORT for the treatment of upper limb spasticity in pediatric patients 2 to 17 years of age was evaluated in a double-blind, low-dose controlled, multicenter study (NCT02106351). A total of 208 patients with spasticity because of cerebral palsy who were toxin naïve or non-naïve (66% had prior treatment with botulinum toxin), weighed at least 10 kgs, and had a baseline Modified Ashworth Score (MAS) of grade 2 or greater (99% patients) at the primary targeted muscle groups (PTMG), were enrolled in the modified Intention to Treat population (mITT). Patients received DYSPORT 16 Units/kg (n=70), DYSPORT 8 Units/kg (n=69), or DYSPORT 2 Units/kg (n=69) injected into the upper limb. The elbow flexors and wrist flexors respectively were the PTMG in 57% and in 43% of patients. The median age of the patients in this study was 9 years (range 2 to 17 years; 57% were between 2 and 9 years of age); 60% of patients were male, and 75% were White.

The primary efficacy endpoint was the mean change from baseline in MAS in the PTMG at Week 6 (see Table 24). The secondary efficacy endpoint was the mean Physician Global Assessment (PGA) score assessed at Week 6 (Table 25). Although PGA scores numerically favored DYSPORT treatment over the low-dose control, the difference was not statistically significant.

Table 24: Modified Ashworth Scale Score in the PTMG Change from Baseline at Week 6 in Pediatric Patients with Upper LImb Spasticity (mITT Population)
 | Control Group | Treatment Groups
 | DYSPORT 2 U/kg (N=69) | DYSPORT 8 U/kg (N=69) | DYSPORT 16 U/kg (N=70)
Baseline
Mean (SD) | 3.1 (0.3) | 3.1 (0.3) | 3.1 (0.5)
Week 6
LSamean change from baseline in PTMGbon MAS | -1.6 | -2.0 | -2.3
Difference from control in LSameans |  | -0.4 | -0.7
p-valuec |  | 0.0118d | <0.0001
Week 16
LSamean change from baseline in PGMGbon MAS | -0.9 | -1.2 | -1.5
Difference from control in LSameans |  | -0.3d | -0.6d

aLS = Least Square
bPTMG=Primary Targeted Muscle Group
cp-value is derived from ANCOVA on ranked MAS score change from baseline with treatment, baseline score, age range at baseline, prior botulinum toxin treatment status at baseline, and center as explanatory variables
dNominal p-value <0.05

Table 25: Physician Global Assessment of Treatment Response at Week 6 in Pediatric Patients with Upper Limb Spasticity (mITT Population)
 | Control Group | Treatment Group
 | DYSPORT 2 U/kg (N=68) | DYSPORT 8 U/kg (N=69) | DYSPORT 16 U/kg (N=70)
Week 6
Mean score (SD) | 1.7 (0.9) | 2.0 (0.9) | 2.0 (0.9)
LSamean in PGA | 1.8 | 2.0 | 2.0
Difference from control in LSamean |  | 0.2 | 0.2
p-valueb |  | 0.2043 | 0.1880
Week 16
Mean score (SD) | 1.7 (1.0) | 1.6 (1.1) | 1.9 (1.2)
LSamean in PGA | 1.8 | 1.7 | 1.9
Difference from contron in LSamean |  | -0.1 | 0.1
p-valueb |  | 0.7001 | 0.4041

aLS=Least Square
bp-value is derived from ANOVA on ranked PGA score with treatment, age range at baseline, prior botulinum toxin treatment status at baseline, and center as explanatory variables

Lower Limb Spasticity in Pediatric Patients
The efficacy of DYSPORT for the treatment of lower limb spasticity in patients 2 to 17 years of age was evaluated in a double-blind, placebo-controlled, multicenter study. A total of 235 patients with cerebral palsy causing dynamic equinus foot deformity who were toxin-naïve or non-naïve and had a Modified Ashworth Score (MAS) of grade 2 or greater at the ankle plantar flexors were enrolled. Patients received DYSPORT 10 Units/kg/leg (n=79), DYSPORT 15 Units/kg/leg (n=79) or placebo (n=77) injected into the gastrocnemius and soleus muscles (see Table 27). Forty-one percent of patients (n=66) were treated bilaterally and received a total lower limb DYSPORT dose of either 20 Units/kg (n=37) or 30 Units/kg (n=29). The median age of the patients in this study was 5 years (range 2 to 17 years); 60% of patients were male, and 73% were Caucasian.
The primary efficacy endpoint was the mean change from baseline in MAS in ankle plantar flexor at Week 4; a co-primary endpoint was the mean Physician’s Global Assessment (PGA) score at Week 4 (see Table 26).

Table 26: MAS and PGA Change from Baseline at Week 4 in Pediatric Patient with Lower Limb Spasticity (ITT Population)
 |  | Placebo (N=77) | DYSPORT 10 Units/kg/leg (N=79) | DYSPORT 15 Units/kg/leg (N=79)
LS Mean Change from Baseline in Ankle plantar flexor Muscle Tone on the MAS | Week 4 | -0.5 | -0.9* | -1.0*
LS Mean Change from Baseline in Ankle plantar flexor Muscle Tone on the MAS | Week 12 | -0.5 | -0.8* | -1.0*
LS Mean PGA of Response to Treatment | Week 4 | 0.7 | 1.5* | 1.5*
LS Mean PGA of Response to Treatment | Week 12 | 0.4 | 0.8* | 1.0*
LS=Least Square
*p‹0.05

16 HOW SUPPLIED/STORAGE AND HANDLING

STORAGE AND HANDLING

DYSPORT® (abobotulinumtoxinA) for Injection is a sterile, lyophilized powder supplied in a single-dose, glass vial. Unopened vials of DYSPORT must be stored refrigerated between 2°C to 8°C (36°F to 46°F). Protect from light.

Do not use after the expiration date on the vial. All vials, including expired vials, or equipment used with DYSPORT should be disposed of carefully as is done with all medical waste.

DYSPORT contains a unique hologram on the carton. If you do not see the hologram, do not use the product. Instead contact 855-463-5127.

Cervical Dystonia, Spasticity in Adults, and Pediatric Patients

500 Unit Vial

Each vial contains 500 Units of freeze-dried abobotulinumtoxinA.
Box containing 1 vial—NDC 15054-0500-1
Box containing 2 vials—NDC 15054-0500-2

300 Unit Vial

Each vial contains 300 Units of freeze-dried abobotulinumtoxinA.
Box containing 1 vial—NDC 15054-0530-6

Glabellar Lines

Each vial contains 300 Units of freeze-dried abobotulinumtoxinA.
Box containing 1 vial— NDC 0299-5962-30

17 PATIENT COUNSELING INFORMATION

Advise the patient to read the FDA-approved patient labeling (Medication Guide).

Swallowing, Speaking, or Breathing Difficulties, or Other Unusual Symptoms
Advise patients to inform their doctor or pharmacist if they develop any unusual symptoms (including difficulty with swallowing, speaking or breathing), or if any known symptom persists or worsens [see Warnings and Precautions (5.1, 5.4)].

Dry Eye with the Treatment of Glabellar Lines
Inform patients that DYSPORT injection may cause eye dryness [see Warnings and Precautions (5.6)]. Advise patients to report symptoms of eye dryness (e.g., eye pain, eye irritation, photosensitivity, or changes in vision) to their doctor.

Ability to Operate Machinery or Vehicles
Inform patients that if loss of strength, muscle weakness, blurred vision or drooping eyelids occur, they should avoid driving a car or engaging in other potentially hazardous activities.

Manufactured by:
Ipsen Biopharm Ltd.
Wrexham, LL13 9UF, UK
U.S. License No. 1787

Distributed by:
Ipsen Biopharmaceuticals, Inc.
Cambridge, MA 02142
and
Galderma Laboratories, L.P.
Dallas, TX 75201 USA

DYSPORT is a registered trademark of Ipsen Biopharm Limited.
© 2023. All rights reserved.

MEDICATION GUIDE
DYSPORT® (DIS-port)
(abobotulinumtoxinA)
for Injection
What is the most important information I should know about DYSPORT?
DYSPORT may cause serious side effects that can be life threatening including:
• Problems breathing or swallowing
• Spread of toxin effects
These problems can happen within hours, or days to weeks after an injection of DYSPORT. Call your doctor or get medical help right away if you have any of these problems after treatment with DYSPORT:

1. Problems swallowing, speaking, or breathing. These problems can happen within hours, or days to weeks after an injection of DYSPORTusually because the muscles that you use to breathe and swallow can become weak after the injection. Death can happen as a complication if you have severe problems with swallowing or breathing after treatment with DYSPORT.
• People with certain breathing problems may need to use muscles in their neck to help them breathe. These patients may be at greater risk for serious breathing problems with DYSPORT.
• Swallowing problems may last for several weeks. People who cannot swallow well may need a feeding tube to receive food and water. If swallowing problems are severe, food or liquids may go into your lungs. People who already have swallowing or breathing problems before receiving DYSPORT have the highest risk of getting these problems.

2. Spread of toxin effects.In some cases, the effect of botulinum toxin may affect areas of the body away from the injection site and cause symptoms of a serious condition called botulism. The symptoms of botulism include:

• loss of strength and muscle weakness all over the body
• blurred vision and drooping eyelids
• trouble saying words clearly (dysarthria)
• trouble breathing
• double vision
• hoarseness or change or loss of voice (dysphonia)
• loss of bladder control
• trouble swallowing

These symptoms can happen within hours, or days to weeks after you receive an injection of DYSPORT.These problems could make it unsafe for you to drive a car or do other dangerous activities. See "What should I avoid while receiving DYSPORT?"

What is DYSPORT?

DYSPORT is a prescription medicine that is injected into muscles and used:

- to treat cervical dystonia (CD) in adults
- to improve the look of moderate to severe frown lines between the eyebrows (glabellar lines) in adults younger than 65 years of age for a short period of time (temporary)
- to treat increased muscle stiffness in people 2 years of age and older with spasticity

It is not known whether DYSPORT is safe or effective in people younger than:

- 18 years of age for the treatment of cervical dystonia
- 18 years of age for the treatment of glabellar lines
- 2 years of age for the treatment of spasticity

It is not known whether DYSPORT is safe or effective for the treatment of other wrinkles.

Who should not take DYSPORT?

Do not take DYSPORT if you:

- are allergic to DYSPORT or any of the ingredients in DYSPORT. See the end of this Medication Guide for a list of ingredients in DYSPORT
- are allergic to cow's milk protein
- had an allergic reaction to any other botulinum toxin product such as Myobloc® (rimabotulinumtoxinB), Botox® (onabotulinumtoxinA), or Xeomin® (incobotulinumtoxinA)
- have a skin infection at the planned injection site

What should I tell my doctor before taking DYSPORT?
Tell your doctor about all your medical conditions, including if you:

- have a disease that affects your muscles and nerves (such as amyotrophic lateral sclerosis [ALS or Lou Gehrig's disease], myasthenia gravis or Lambert-Eaton syndrome). See "What is the most important information I should know about DYSPORT?"
- have allergies to any botulinum toxin product
- had any side effect from botulinum toxin product in the past
- have or have had a breathing problem, such as asthma or emphysema
- have or have had swallowing problems
- have or have had bleeding problems
- have diabetes
- have or have had a slow heart beat or other problem with your heart rate or rhythm
- have plans to have surgery
- had surgery on your face
- have weakness in or near your muscles being treated
- have drooping eyelids
- experienced dry eye with previous use of botulinum toxin products
- have any other change in the way your face normally looks
- are pregnant or plan to become pregnant. It is not known if DYSPORT can harm your unborn baby
- are breast-feeding or planning to breast-feed. It is not known if DYSPORT passes into breast milk

Tell your doctor about all the medicines you take, including prescription and over-the-counter medicines, vitamins and herbal products. Using DYSPORT with certain other medicines may cause serious side effects.

Do not start any new medicines until you have told your doctor that you have received DYSPORT in the past.
Especially tell your doctor if you:

- have received any other botulinum toxin product in the last four months
- have received injections of botulinum toxin, such as Myobloc® (rimabotulinumtoxinB), Botox® (onabotulinumtoxinA) or Xeomin® (incobotulinumtoxinA) in the past; be sure your doctor knows exactly which product you received
- have recently received an antibiotic by injection
- take muscle relaxants
- take an allergy or cold medicine
- take a sleep medicine

Ask your doctor if you are not sure if your medicine is one that is listed above.

Know the medicines you take. Keep a list of your medicines with you to show your doctor and pharmacist each time you get a new medicine.

How will I receive DYSPORT?

- DYSPORT is an injection that your doctor will give you
- DYSPORT is injected into the affected muscles
- If you are and adult, your doctor may give you another dose of DYSPORT after 12 weeks or longer, if it is needed
- If you are an adult being treated for CD or spasticity or you are a child (2 to 17 years of age) being treated for spasticity, your doctor may change your dose of DYSPORT, until you and your doctor find the best dose for you. Children should not be retreated sooner than every 12 - 16 weeks.
- The dose of DYSPORT is not the same as the dose of any other botulinum toxin product

What should I avoid while receiving DYSPORT?

DYSPORT may cause loss of strength or general muscle weakness, blurred vision, or drooping eyelids within hours to weeks of taking DYSPORT. If this happens, do not drive a car, operate machinery, or do other dangerous activities. See "What is the most important information I should know about DYSPORT?"

What are the possible side effects of DYSPORT?

DYSPORT can cause serious side effects. See "What is the most important information I should know about DYSPORT?"

The most common side effects of DYSPORT in people with cervical dystonia include:

- muscle weakness
- dry mouth
- feeling of tiredness
- muscle pain
- problems speaking
- eye problems
- difficulty swallowing
- injection site pain or discomfort
- headache

The most common side effects of DYSPORT in people with glabellar lines include:

- stuffy or runny nose and sore throat
- injection site pain
- upper respiratory infection
- blood in urine
- headache
- injection site reaction
- swelling of eyelids
- drooping eyelids
- sinus infection
- nausea

The most common side effects of DYSPORT in adults with upper limb spasticity include:

• muscle weakness

The most common side effects of DYSPORTin adults with lower limb spasticity include:

- muscle weakness
- pain in your arms or legs
- fall

The most common side effects of DYSPORT in children (2 to 17 years of age) with upper limb spasticity include:

- upper respiratory tract infection
- sore throat

The most common side effects of DYSPORT in children (2 to 17 years of age) with lower limb spasticity include:

- stuffy or runny nose and sore throat
- cough
- fever

Tell your doctor if you have any side effect that bothers you or that does not go away. These are not all the possible side effects DYSPORT. For more information, ask your doctor or pharmacist.

Tell your doctor if you have dry eye or changes in vision following use of DYSPORT.

Call your doctor for medical advice about side effects. You may report side effects to FDA at 1-800-FDA-1088.

General information about DYSPORT:

Medicines are sometimes prescribed for purposes other than those listed in a Medication Guide.

This Medication Guide summarizes the most important information about DYSPORT. If you would like more information, talk with your doctor. You can ask your doctor or pharmacist for information about DYSPORT that is written for healthcare professionals.

What are the ingredients in DYSPORT?

Active ingredient: (botulinum toxin Type A)
Inactive ingredients: human albumin and lactose. DYSPORT may contain cow's milk protein.

Distributed by: Ipsen Biopharmaceuticals, Inc. Cambridge, MA 02142 and Galderma Laboratories, L.P. Dallas, TX 75201
Manufactured by: Ipsen Biopharma Ltd., Wrexham, LL13 9UF, UK U.S. License No. 1787
For more information about DYSPORT, call 855-463-5127 or go to www.dysport.comor www.DysportUSA.com.
This Medication Guide has been approved by the U.S. Food and Drug Administration

Revised 09/2023
DYSPORT is a registered trademark of Ipsen Biopharm Limited. Botox, Xeomin and Myobloc are registered trademarks of their respective owners.
© 2023. All rights reserved.

PRINCIPAL DISPLAY PANEL - 300 UNIT

GALDERMA
Dysport® (AbobotulinumtoxinA)
for injection
For intramuscular use

300 UNITS/SINGLE-DOSE VIAL

1 VIAL

WARNING: Dosing units of botulinum toxins are not interchangeable between commercial products

NDC 0299-5962-30

Rx only